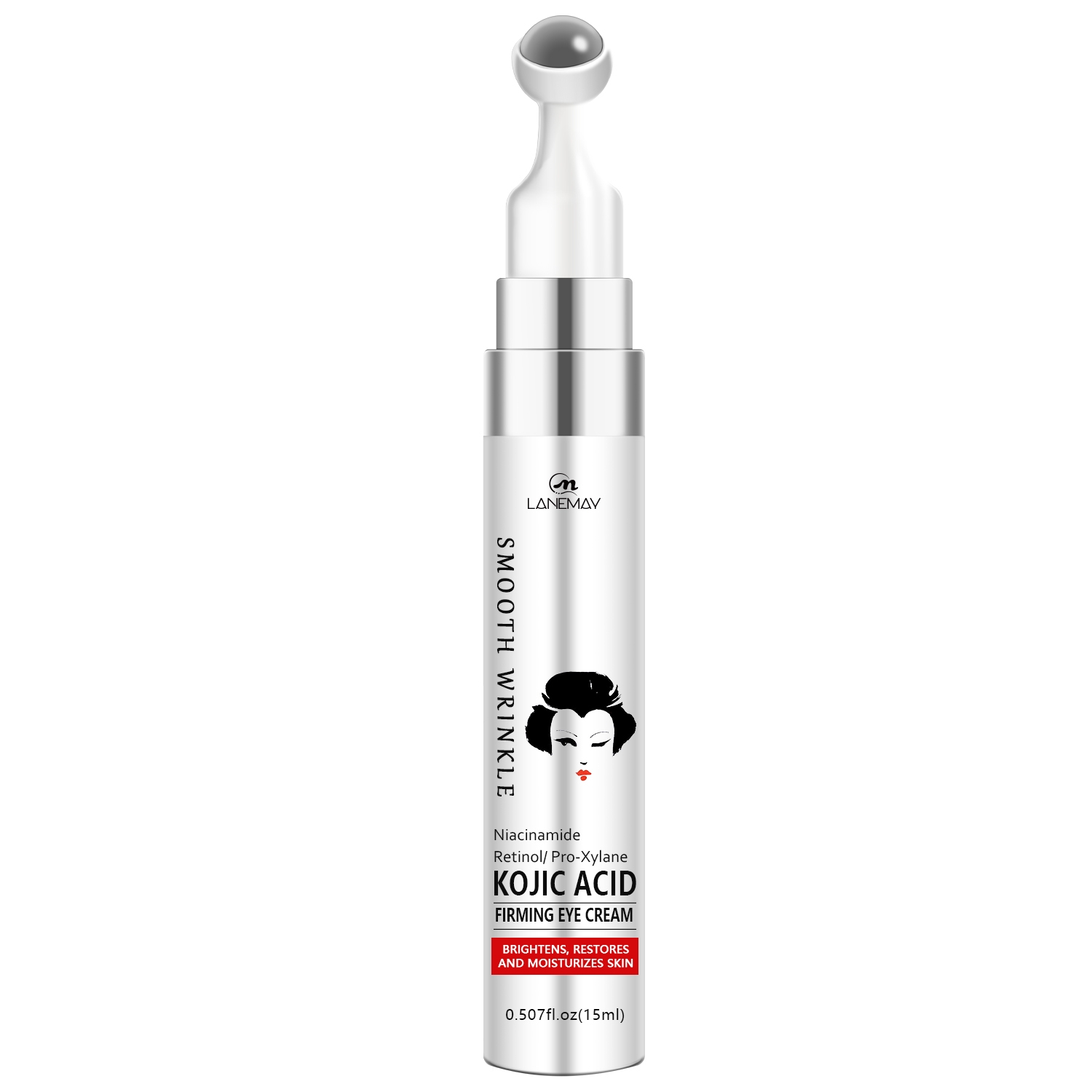 DRUG LABEL: Kojic Acid Firming Eye Cream
NDC: 84025-211 | Form: CREAM
Manufacturer: Guangzhou Yanxi Biotechnology Co., Ltd
Category: otc | Type: HUMAN OTC DRUG LABEL
Date: 20241014

ACTIVE INGREDIENTS: CETYL ETHYLHEXANOATE 2 mg/15 mL; GLYCERIN 3 mg/15 mL
INACTIVE INGREDIENTS: WATER

DOSAGE AND ADMINISTRATION

Gently dlspense up to one pump and dot around eye area.Massage product onto skin using coollng metal appllcator.

WARNINGS

keep out of children

INACTIVE INGREDIENT

Aqua

INDICATIONS AND USAGE

Daily skin care around the eyes

keep out of children

PURPOSE

skin moisturizing